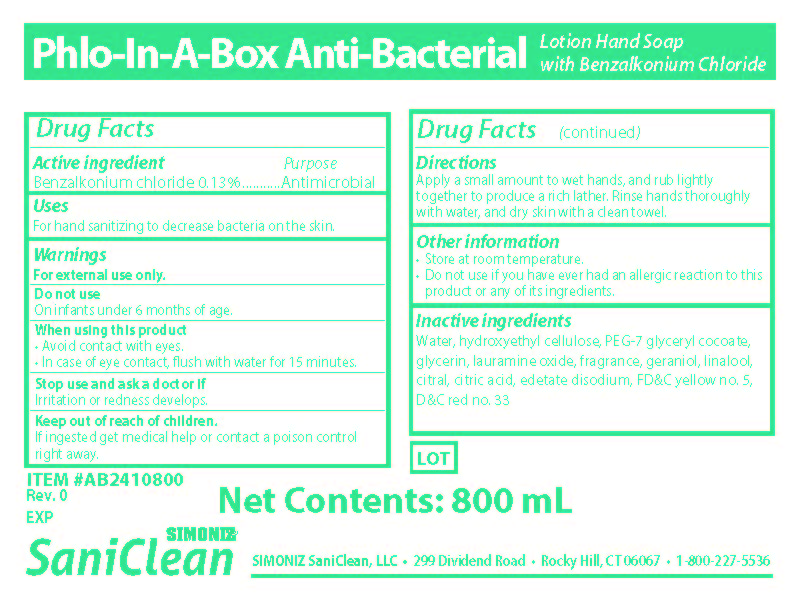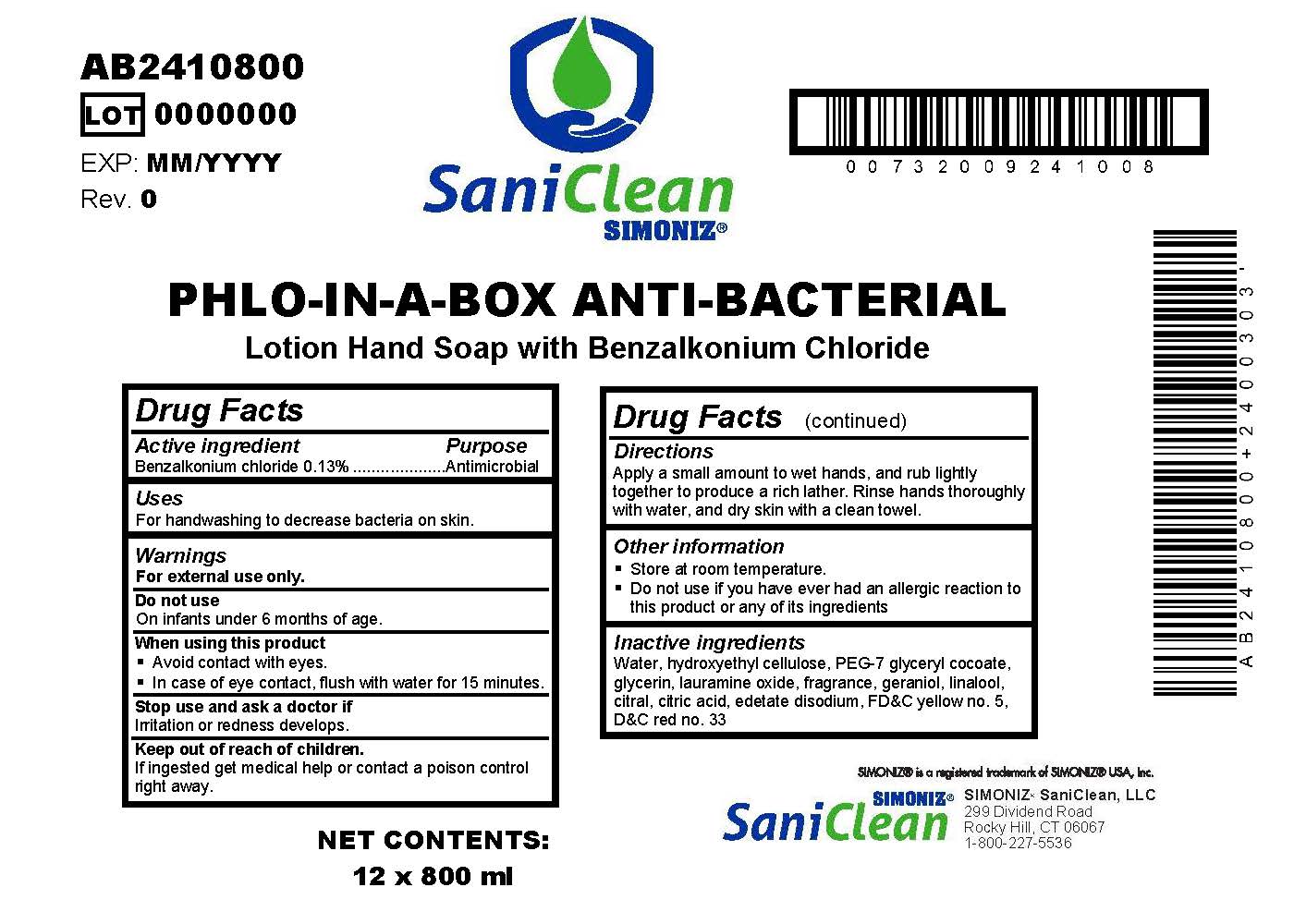 DRUG LABEL: Saniclean
NDC: 63900-120 | Form: SOAP
Manufacturer: Simoniz Saniclean, LLC
Category: otc | Type: HUMAN OTC DRUG LABEL
Date: 20251105

ACTIVE INGREDIENTS: BENZALKONIUM CHLORIDE 0.14 g/100 mL
INACTIVE INGREDIENTS: LINALOOL, (+/-)-; LAURAMINE OXIDE; ANHYDROUS CITRIC ACID; GLYCERIN; D&C RED NO. 33; EDETATE DISODIUM; HYDROXYETHYL CELLULOSE, UNSPECIFIED; FD&C YELLOW NO. 5; CITRAL; PEG-7 GLYCERYL COCOATE; WATER; GERANIOL

Phlo-In-A-Box Anti-Bacterial
Lotion Hand Soap with 0.13% Benzalkonium Chloride

Active ingredient

Benzalkonium chloride 0.13%

Purpose

Antimicrobial

Uses
For handwashing to decrease bacteria on skin.

Warnings

For external use only.

Do not use

On infants under 6 months of age.

When using this product

- Avoid contact with eyes.
- In case of eye contact, flush with water for 15 minutes.

Stop use and ask a doctor if

Irritation or redness develops.

Keep out of reach of children.

If ingested get medical help or contact a poison control right away.

Directions
Apply a small amount to wet hands, and rub lightly together to produce a rich lather. Rinse hands thoroughly with water, and dry skin with a clean towel.

Other information

- Store at room temperature.
- Do not use if you have ever had an allergic reaction to this product or any of its ingredients

INACTIVE INGREDIENT

Inactive ingredientsWater, hydroxyethyl cellulose, PEG-7 glyceryl cocoate, glycerin, lauramine oxide, fragrance, geraniol, linalool, citral, citric acid, edetate disodium, FD&C yellow no. 5, D&C red no. 33

Simoniz Saniclean, LLC

299 Dividend Road

Rocky Hill, CT 06067

1-800-227-5536

800 mL Bags

PHLO-IN-A-BOX ANTI-BACTERIAL
Lotion Hand Soap with Benzalkonium Chloride

Net Contents: 800 ml

Simoniz Saniclean, LLC 299 Dividend Road Rocky Hill, CT 06067 1-800-227-5536